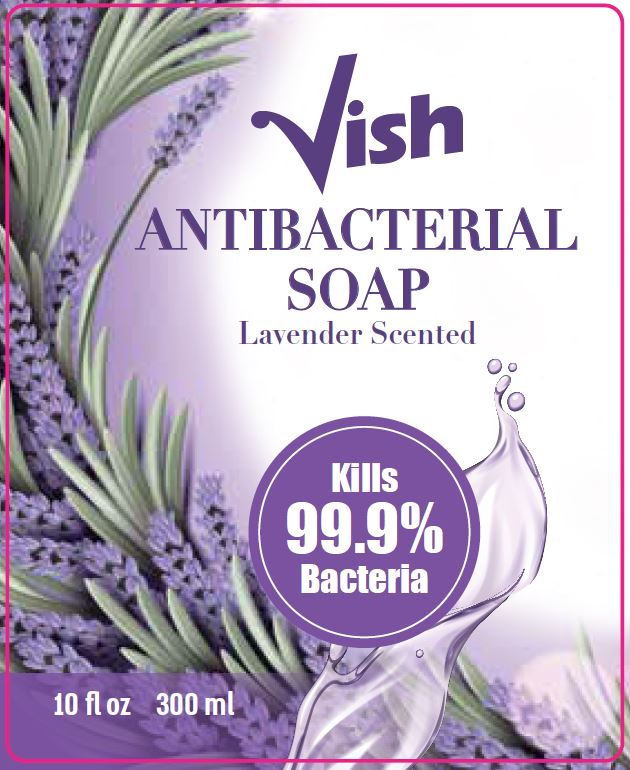 DRUG LABEL: Lavender Antibacterial
NDC: 62685-120 | Form: SOAP
Manufacturer: Tropical Degil Cosmetics Industries LTD
Category: otc | Type: HUMAN OTC DRUG LABEL
Date: 20200901

ACTIVE INGREDIENTS: BENZALKONIUM CHLORIDE 0.1755 g/135 g
INACTIVE INGREDIENTS: GLYCERIN; METHYLCHLOROISOTHIAZOLINONE; CETRIMONIUM CHLORIDE; COCO MONOETHANOLAMIDE; METHYLISOTHIAZOLINONE; FD&C RED NO. 4; LAURAMINE OXIDE; PEG-120 METHYL GLUCOSE DIOLEATE; COCAMIDOPROPYLAMINE OXIDE; SODIUM CHLORIDE; D&C VIOLET NO. 2; WATER

Tropical Degil lavender antibacterial soap

Active ingredient

Benzalkonium Chloride 0.13%

Purpose

Antibacterial

Uses

For handwashing to decrease bacteria on the skin.

Warnings

For external use only.

When using this product avoid contact with eyes. In case of contact with eyes, rinse eyes thoroughly with water.

Stop use and ask a doctor if

irritaion or redness develops.

Keep out of reach of children. If swallowed, get medical help or contact a Poiston Control Center right away.

Directions

- Pump into hands, wet as needed
- Lather for at least 15 seconds
- Rinse and dry thoroughly

Inactive ingredients

Cetrimonium Chloride, Cocamide MEA, Cocamidopropylamine Oxide, Fragrance, Glycerin, Lauramine Oxide, Methylchloroisothiazolinone, Methylisothiazolinone, PEG-120 Methyl Glucose Dioleate, Sodium Chloride, Red 4, Violet 2, Water.

Prinicpal Display Panel

Antibacterial Soap

Lavender Scented

10 fl oz 300 ml